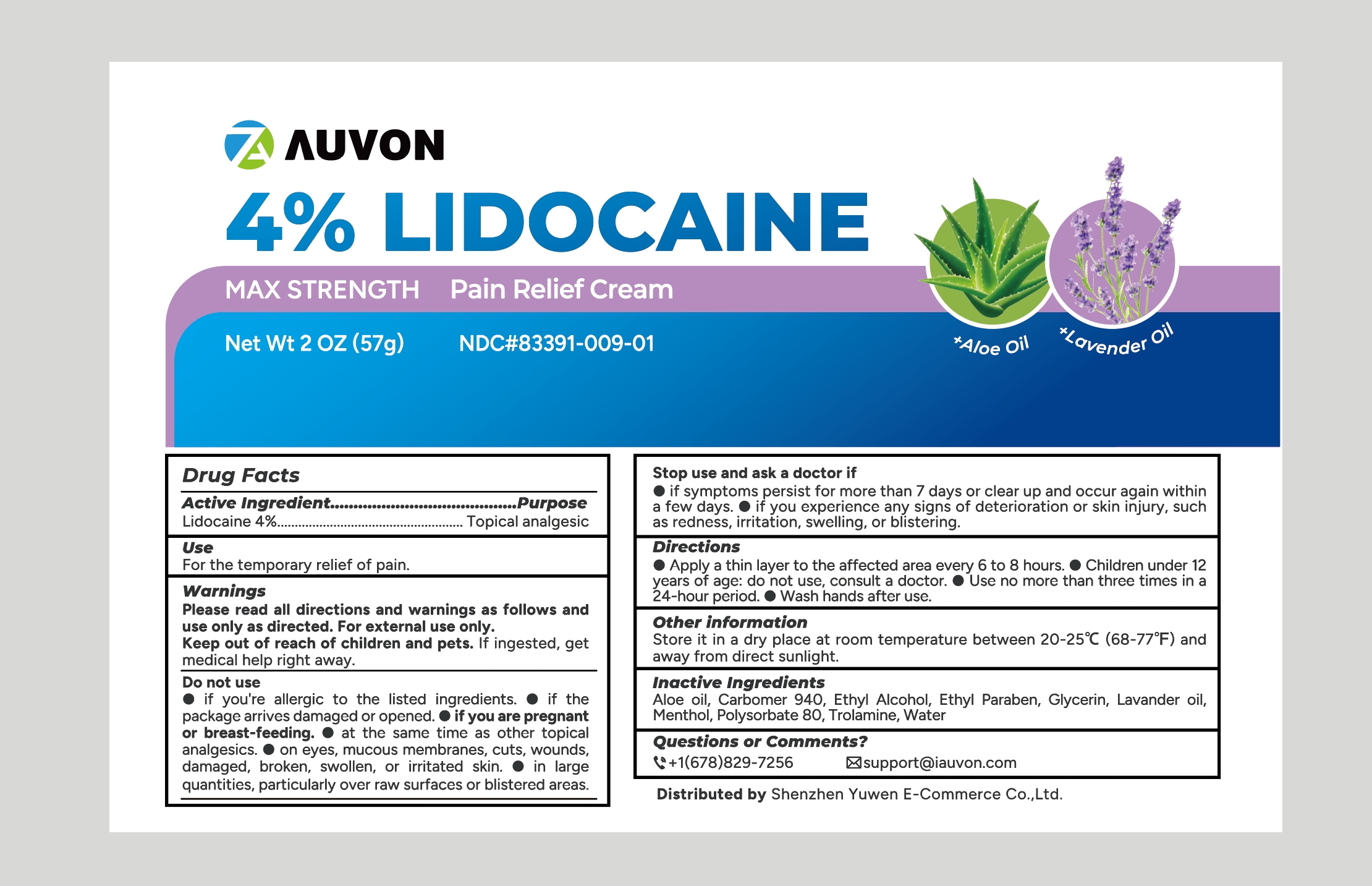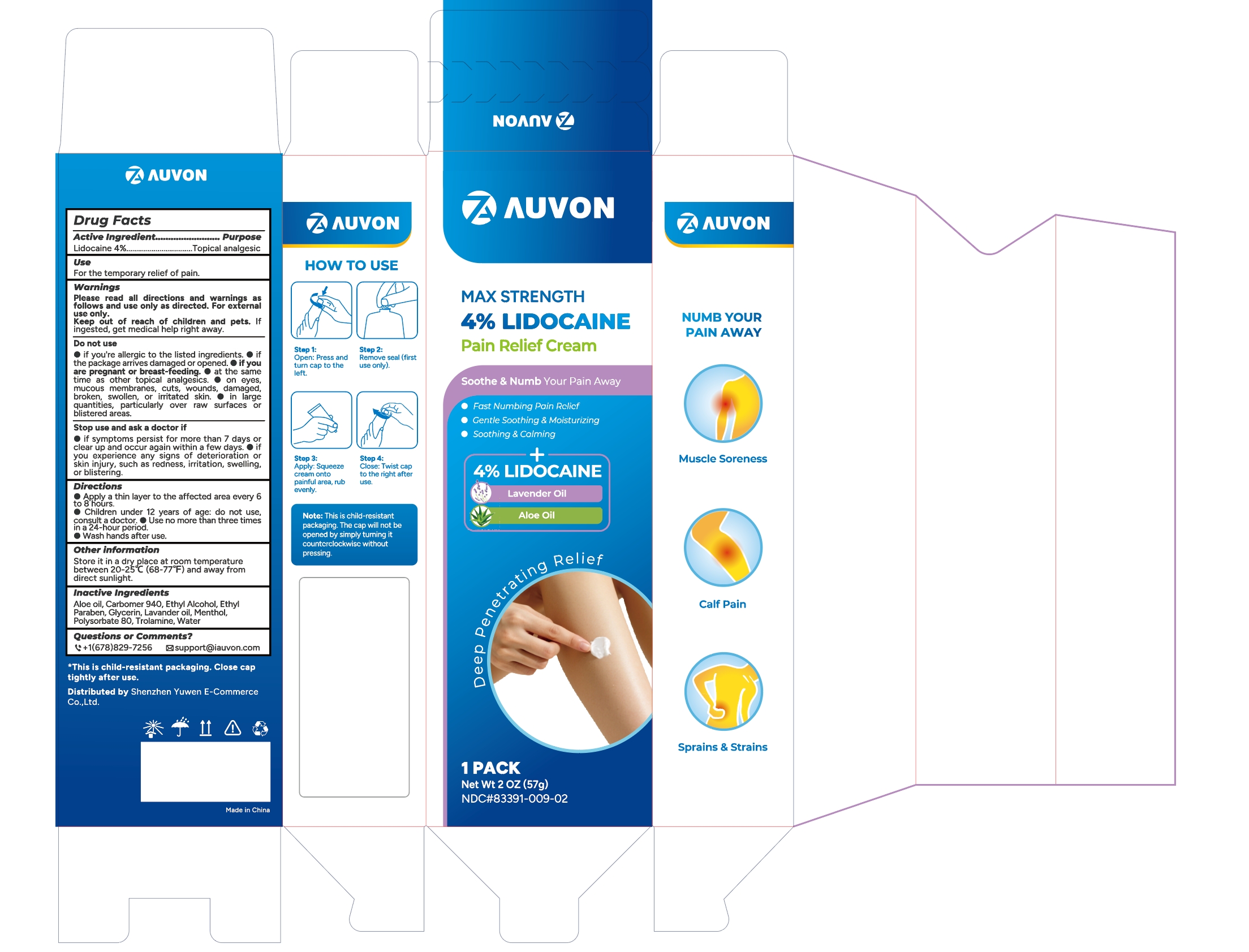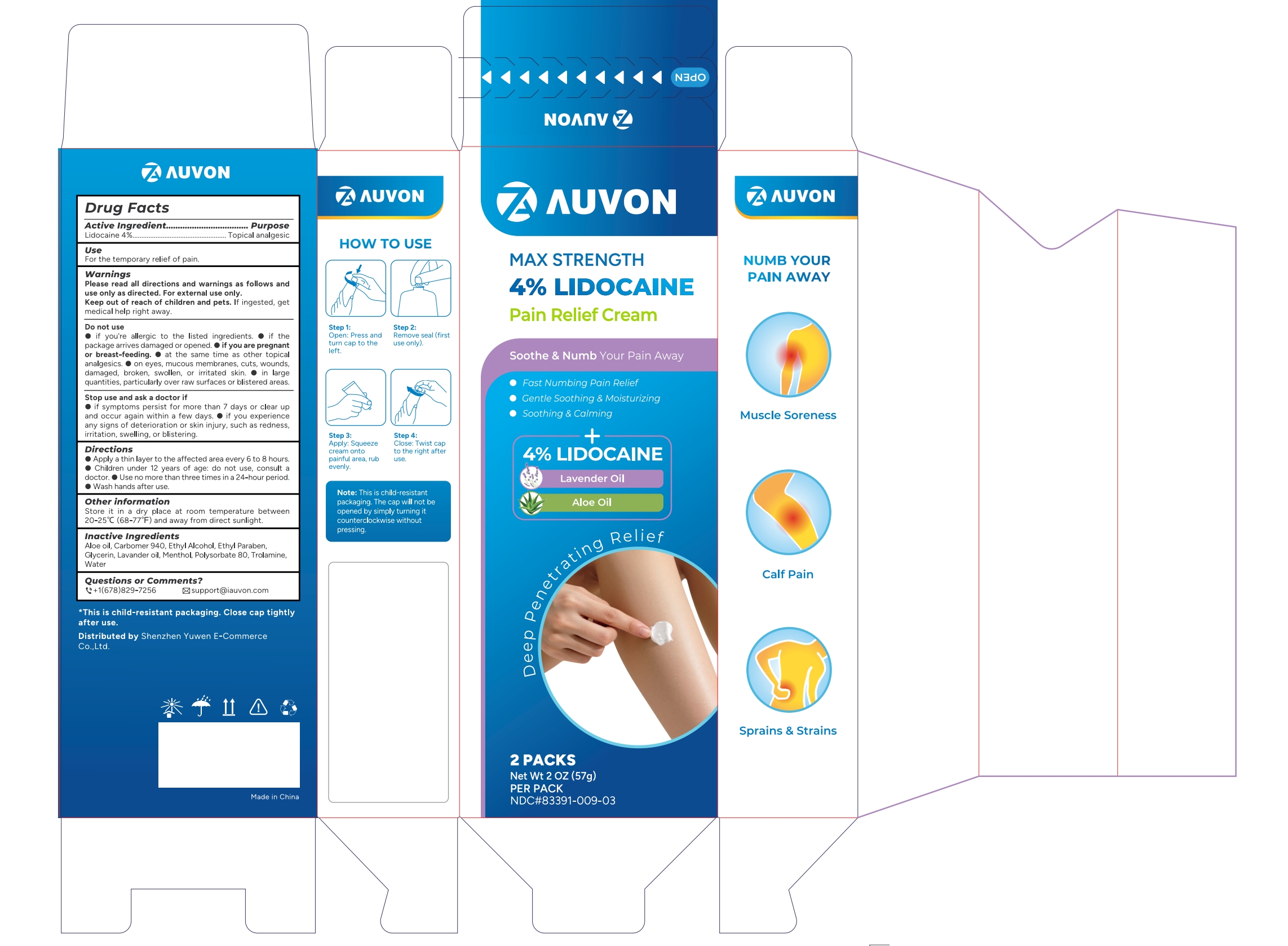 DRUG LABEL: AUVON Pain Relief Cream
NDC: 83391-009 | Form: CREAM
Manufacturer: SHENZHEN YUWEN E-COMMERCE CO., LTD.
Category: otc | Type: HUMAN OTC DRUG LABEL
Date: 20250522

ACTIVE INGREDIENTS: LIDOCAINE 4 g/100 g
INACTIVE INGREDIENTS: WATER; ALCOHOL; LAVENDER OIL; POLYSORBATE 80; ALOE VERA LEAF OIL; TROLAMINE; GLYCERIN; ETHYLPARABEN; RACEMENTHOL; CARBOMER 940

83391-009

Drug Facts

ACTIVE INGREDIENT

Lidocaine 4%

PURPOSE

Topical Analgestic

INDICATIONS AND USAGE

For the temporay relief of pain

WARNINGS

Please read all directions and warnings as follows and use only as directed. For external use only.
Keep out of reach of children and pets. If ingested, get medical help right away.

Do not use

if you're allergic to the listed ingredients.

if the package arrives damaged or opened.

if you are pregnant or breast-feeding.

at the same time as other topical analgesics.

on eyes, mucous membranes, cuts, wounds damaged, broken, swolen. or irritated skin.

In large quantities. particularly over raw surfaces or blistered area

Stop use and ask a doctor
if symptoms persist for more than / days or clear up and occur again within a few davs.

if you experience any signs of deterioration or skin iniurv. such as redness, irritation, sweling, or bistering.

Keep out of reach of children and pets. If ingested, get medical help right away.

DOSAGE AND ADMINISTRATION

Apply a thin layer to the affected area every 6 to 8 hours.

Children under 12 years of age:do not use, consult a doctor.

Use no more than three times in a day.

Wash hands after use.

STORAGE AND HANDLING

Store it in a dry place at room temperature between 20-25°C (68-77°F) and away from direct sunlight.

INACTIVE INGREDIENT

Aloe oil, Carbomer 940, Ethyl Alcohol, Ethyl Paraben, Glycerin, Lavander oil,
Menthol, Polysorbate 80, Trolamine, Water